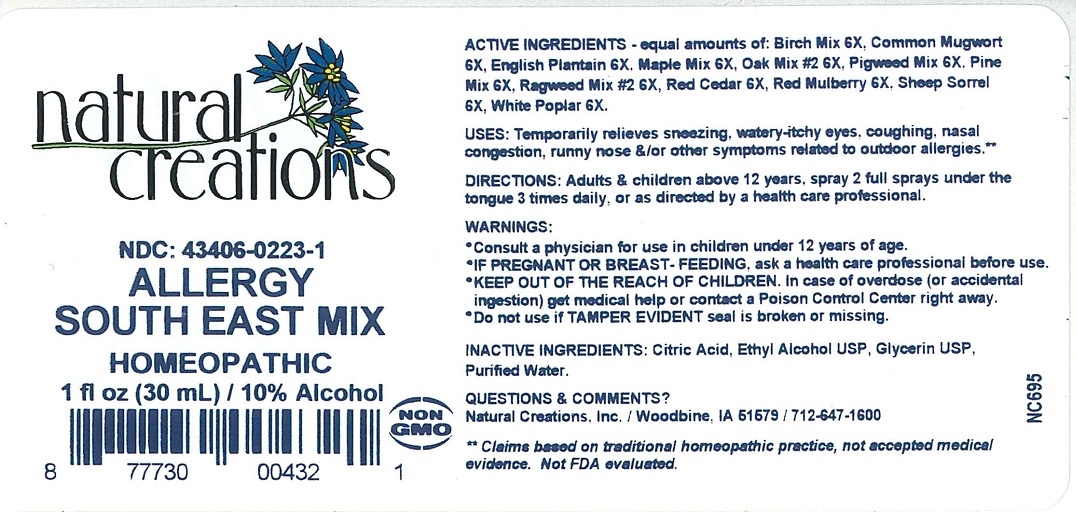 DRUG LABEL: ALLERGY SOUTH EAST MIX
NDC: 43406-0223 | Form: LIQUID
Manufacturer: Natural Creations, Inc
Category: homeopathic | Type: HUMAN OTC DRUG LABEL
Date: 20251103

ACTIVE INGREDIENTS: BETULA PENDULA WHOLE 6 [hp_X]/1 mL; ARTEMISIA VULGARIS POLLEN 6 [hp_X]/1 mL; PLANTAGO LANCEOLATA POLLEN 6 [hp_X]/1 mL; ACER NEGUNDO WOOD 6 [hp_X]/1 mL; QUERCUS SPP. WHOLE 6 [hp_X]/1 mL; CHENOPODIUM ALBUM WHOLE 6 [hp_X]/1 mL; PINUS SPP. WHOLE 6 [hp_X]/1 mL; AMBROSIA CONFERTIFLORA WHOLE 6 [hp_X]/1 mL; JUNIPERUS VIRGINIANA POLLEN 6 [hp_X]/1 mL; MORUS RUBRA WHOLE 6 [hp_X]/1 mL; RUMEX ACETOSELLA WHOLE 6 [hp_X]/1 mL; POPULUS ALBA WHOLE 6 [hp_X]/1 mL
INACTIVE INGREDIENTS: CITRIC ACID ACETATE; ALCOHOL; GLYCERIN; WATER

ALLERGY SOUTH EAST MIX

ACTIVE INGREDIENT

ACTIVE INGREDIENTS - equal amount of: Birch mix 6X, Common Mugwort 6X, English Plantain 6X, Maple Mix 6X, Oak Mix #2 6X, Pigweed Mix 6X, Pine Mix 6X, Ragweed Mix #2 6X, Red Cedar 6X, Red Mulberry 6X, Sheep Sorrel 6X, White Poplar 6X.

INDICATIONS AND USAGE

USES: Temporarily relieves sneezing, watery-itchy eyes, coughing, nasal congestion, runny nose &/or other symptoms related to outdoor allergies.**

PURPOSE

USES: Temporarily relieves sneezing, watery-itchy eyes, coughing, nasal congestion, runny nose &/or other symptoms related to outdoor allergies.**

DOSAGE AND ADMINISTRATION

DIRECTIONS: Adults & children above 12 years, spray 2 full sprays under the tongue 3 times daily, or as directed by a health care professional.

KEEP OUT OF REACH OF CHILDREN

KEEP OUT OF THE REACH OF CHILDREN. In case of overdose (or accidental ingestion) get medical help or contact a Poison Control Center right away.

WARNINGS:

- Consult a physician for use in children under 12 years of age.
- IF PREGNANT OR BREAST-FEEDING, ask a health care professional before use.
- KEEP OUT OF THE REACH OF CHILDREN. In case of overdose (or accidental ingestion) get medical help or contact a Poison Control Center right away.
- Do not use if TAMPER EVIDENT seal is broken or missing.

INACTIVE INGREDIENT

INACTIVE INGREDIENTS: Citric Acid, Ethyl Alcohol USP, Glycerin USP, Purified Water.

QUESTIONS & COMMENTS?

Natural Creations, Inc. / Woodbine, IA 51579 / 712-647-1600

REFERENCES

**Claims based on traditional homeopathic practice, not accepted medical evidence. Not FDA evaluated.

PACKAGE LABEL

NDC: 43406-0223-1

ALLERGY SOUTH EAST MIX

HOMEOPATHIC

1 fl oz (30 mL) / 10% Alcohol

877730004321